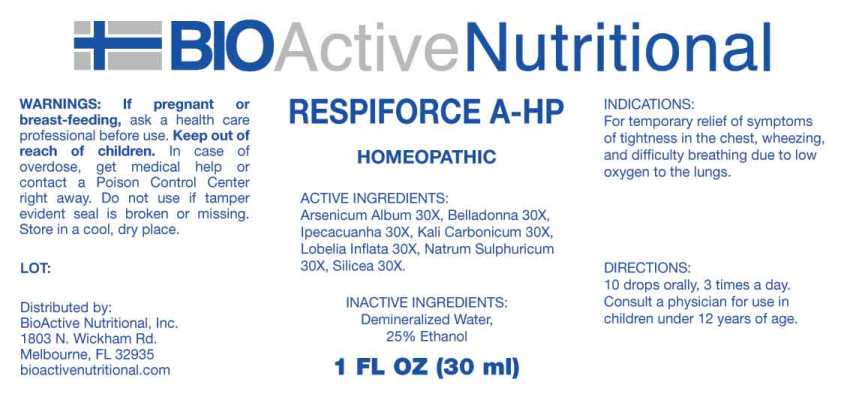 DRUG LABEL: Respiforce A-HP
NDC: 43857-0612 | Form: LIQUID
Manufacturer: BioActive Nutritional, Inc.
Category: homeopathic | Type: HUMAN OTC DRUG LABEL
Date: 20230616

ACTIVE INGREDIENTS: ARSENIC TRIOXIDE 30 [hp_X]/1 mL; ATROPA BELLADONNA 30 [hp_X]/1 mL; IPECAC 30 [hp_X]/1 mL; POTASSIUM CARBONATE 30 [hp_X]/1 mL; LOBELIA INFLATA WHOLE 30 [hp_X]/1 mL; SODIUM SULFATE 30 [hp_X]/1 mL; SILICON DIOXIDE 30 [hp_X]/1 mL
INACTIVE INGREDIENTS: WATER; ALCOHOL

DRUG FACTS:

ACTIVE INGREDIENTS:

Arsenicum Album 30X, Belladonna 30X, Ipecacuanha 30X, Kali Carbonicum 30X, Lobelia Inflata 30X, Natrum Sulphuricum 30X, Silicea 30X.

INDICATIONS:

For temporary relief of symptoms of tightness in the chest, wheezing, and difficulty breathing due to low oxygen to the lungs.

WARNINGS:

If pregnant or breast-feeding, ask a health care professional before use.

Keep out of reach of children. In case of overdose, get medical help or contact a Poison Control Center right away.

Do no use if tamper evident seal is broken or missing.

Store in cool, dry place.

Keep out of reach of children. In case of overdose, get medical help or contact a Poison Control Center right away.

DIRECTIONS:

10 drops orally, 3 times a day. Consult a physician for use in children under 12 years of age.

INDICATIONS:

For temporary relief of symptoms of tightness in the chest, wheezing, and difficulty breathing due to low oxygen to the lungs.

INACTIVE INGREDIENTS:

Demineralized Water, 25% Ethanol

QUESTIONS:

Distributed by:

BioActive Nutritional, Inc.

1803 N. Wickham Rd.

Melbourne, FL 32935

bioactivenutritional.com

PACKAGE DISPLAY LABEL:

BioActiveNutritional

RESPIFORCE A-HP

HOMEOPATHIC

1 FL OZ (30 mL)